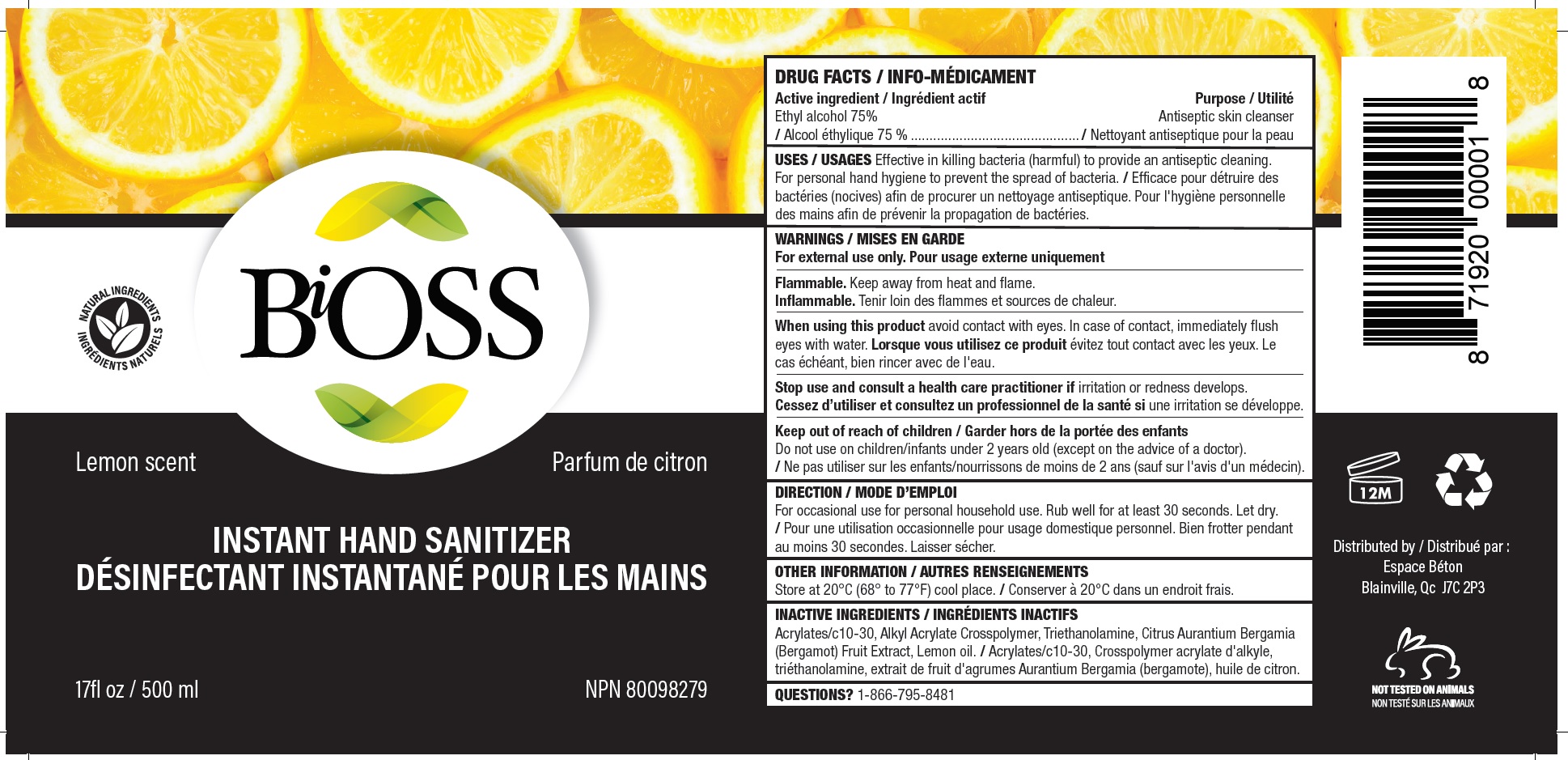 DRUG LABEL: BiOSS Hand Sanitizer
NDC: 77134-000 | Form: GEL
Manufacturer: Bioss Inc.
Category: otc | Type: HUMAN OTC DRUG LABEL
Date: 20200519

ACTIVE INGREDIENTS: ALCOHOL 0.75 mL/1 mL
INACTIVE INGREDIENTS: CARBOMER INTERPOLYMER TYPE A (ALLYL SUCROSE CROSSLINKED); TROLAMINE; BERGAMOT OIL; LEMON OIL

BiOSS Hand Sanitizer Lemon Scent

Active ingredient

Ethyl alcohol 75%

Purpose

Antiseptic skin cleanser

USES

Effective in killing bacteria (harmful) to provide an antiseptic cleaning. For personal hand hygiene to prevent the spread of bacteria.

WARNINGS

For external use only.

Flammable. Keep away from heat and flame.

When using this product

avoid contact with eyes. In case of contact, immediately flush eyes with water.

Stop use and consult a health care practitioner if

irritation or redness develops.

Keep out of reach of children

Do not use on children/infants under 2 years old (except on the advice of a doctor).

DIRECTION

For occasional use for personal household use. Rub well for at least 30 seconds. Let dry.

OTHER INFORMATION

Store at 20°C (68° to 77°F) cool place.

INACTIVE INGREDIENTS

Acrylates/c10-30, Alkyl Acrylate Crosspolymer, Triethanolamine, Citrus Aurantium Bergamia (Bergamot) Fruit Extract, Lemon oil.

QUESTIONS?

1-866-795-8481